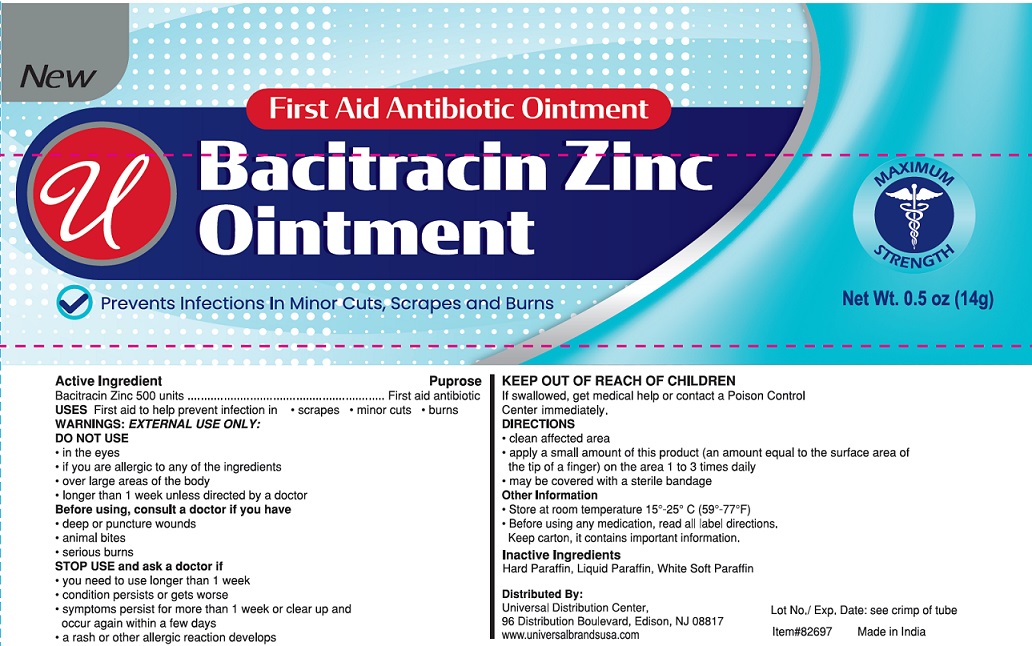 DRUG LABEL: Bacitracin Zinc
NDC: 52000-059 | Form: OINTMENT
Manufacturer: Universal Distribution Center LLC
Category: otc | Type: HUMAN OTC DRUG LABEL
Date: 20251030

ACTIVE INGREDIENTS: BACITRACIN ZINC 500 [USP'U]/1 g
INACTIVE INGREDIENTS: PARAFFIN; MINERAL OIL; WHITE PETROLATUM

Bacitracin Zinc Ointment

Active Ingredient

Bacitracin Zinc 500 units

Purpose

First aid antibiotic

USES

First aid to help prevent infection in

- scrapes
- minor cuts
- burns

WARNINGS

EXTERNAL USE ONLY

DO NOT USE

- in the eyes
- if you are allergic to any of the ingredients
- over large areas of the body
- longer than 1 week unless directed by a doctor

Before using, consult a doctor if you have

- deep or puncture wounds
- animal bites
- serious burns

STOP USE and ask a doctor if

- you need to use longer than 1 week
- condition persists or gets worse
- symptoms persists for more than 1 week or clear up and occur again within a few days
- a rash or other allergic reaction develops

KEEP OUT OF REACH OF CHILDREN

If swallowed get medical help or contact a Poison Control Center immediately.

DIRECTIONS

- clean affected area
- apply a small amount of this product (an amount equal to the surface area of the tip of a finger) on the area 1 to 3 times daily
- may be covered with a sterile bandage

Other information

- Store at room temperature 15° to 25°C (59° to 77°F).
- Before using any medication, read all label directions.

Keep carton, it contains important information.

Lot No./Exp. Date: see crimp of tube.

Inactive Ingredients

Hard Paraffin, Liquid Paraffin, White Soft Paraffin

PRINCIPAL DISPLAY PANEL

Bacitracin Zinc Ointment
NET WT 0.5 OZ (14g)